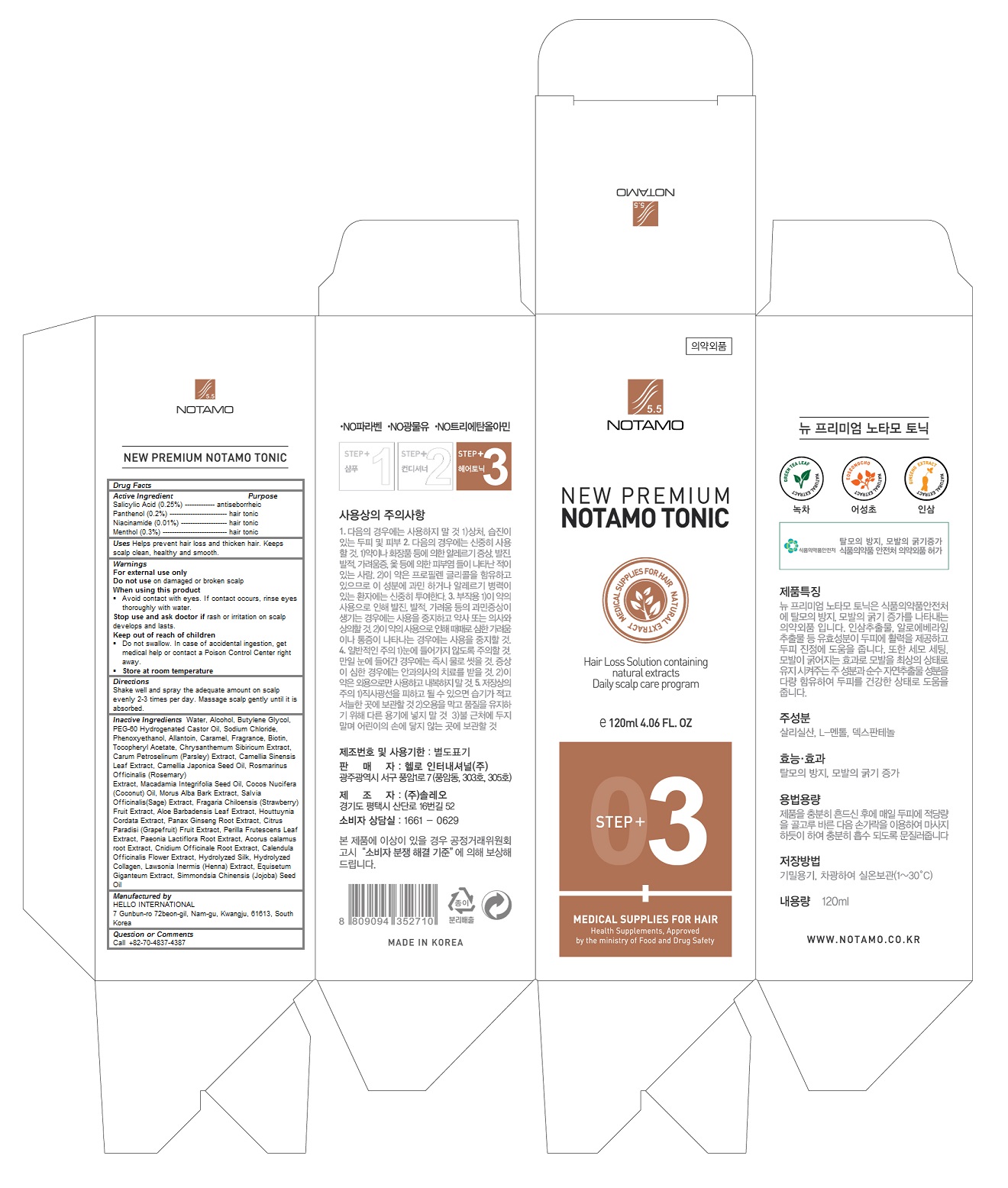 DRUG LABEL: New Premium Notamo Tonic
NDC: 69709-106 | Form: LIQUID
Manufacturer: HELLO INTERNATIONAL
Category: otc | Type: HUMAN OTC DRUG LABEL
Date: 20160504

ACTIVE INGREDIENTS: Panthenol 0.002 1/120 mL; Niacinamide 0.0001 1/120 mL; Menthol 0.003 1/120 mL; Salicylic Acid 0.0025 1/120 mL
INACTIVE INGREDIENTS: water; ALCOHOL; Butylene Glycol; PEG-60 HYDROGENATED CASTOR OIL; Sodium Chloride; PHENOXYETHANOL; Allantoin; Caramel; Biotin; .ALPHA.-TOCOPHEROL ACETATE; PETROSELINUM CRISPUM; GREEN TEA LEAF; CAMELLIA JAPONICA SEED OIL; ROSEMARY; MACADAMIA OIL; COCONUT OIL; MORUS ALBA BARK; SALVIA OFFICINALIS ROOT; BEACH STRAWBERRY; ALOE VERA LEAF; HOUTTUYNIA CORDATA FLOWERING TOP; ASIAN GINSENG; GRAPEFRUIT; PERILLA FRUTESCENS TOP; PAEONIA LACTIFLORA ROOT; ACORUS CALAMUS ROOT; CNIDIUM OFFICINALE ROOT; CALENDULA OFFICINALIS FLOWER; JOJOBA OIL

New Premium Notamo Tonic